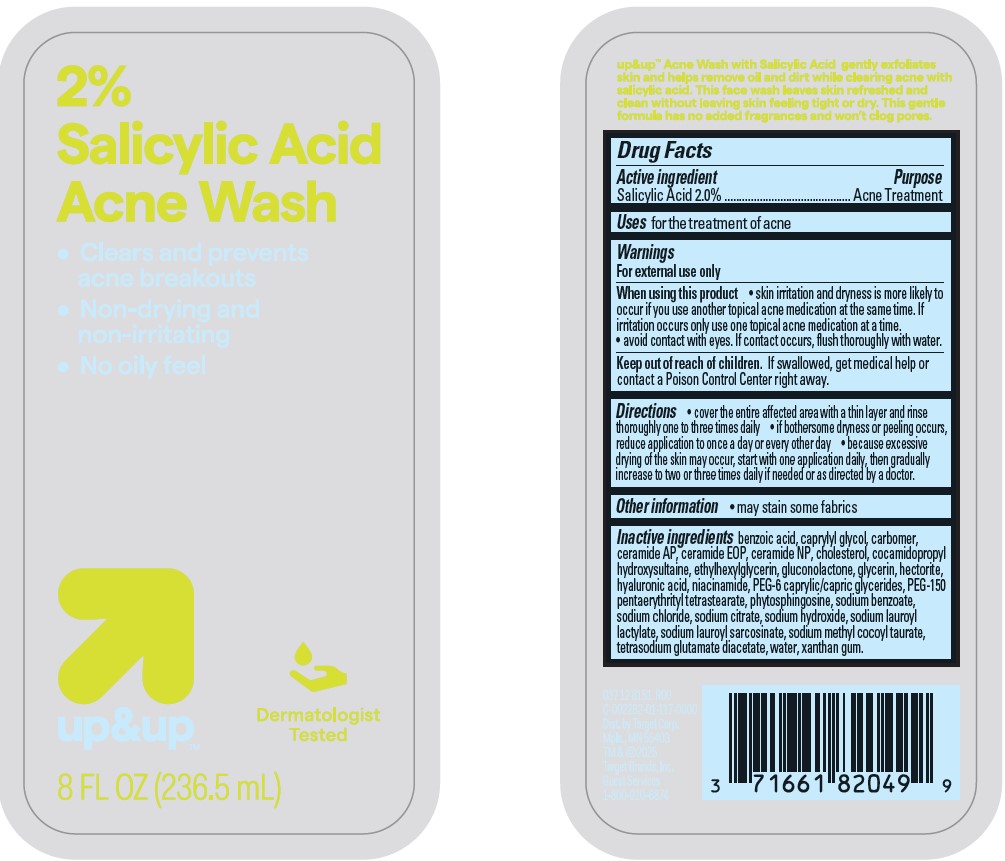 DRUG LABEL: Target Up and Up Salicylic Acid Acne Wash
NDC: 82442-014 | Form: LIQUID
Manufacturer: TARGET CORPORATION
Category: otc | Type: HUMAN OTC DRUG LABEL
Date: 20240930

ACTIVE INGREDIENTS: SALICYLIC ACID 20 mg/1 mL
INACTIVE INGREDIENTS: PEG-150 PENTAERYTHRITYL TETRASTEARATE; GLYCERIN; CHOLESTEROL; XANTHAN GUM; NIACINAMIDE; HYALURONIC ACID; POLYACRYLIC ACID (250000 MW); SODIUM CITRATE; SODIUM HYDROXIDE; CARBOMER INTERPOLYMER TYPE A (ALLYL SUCROSE CROSSLINKED); SODIUM BENZOATE; SODIUM LAUROYL LACTYLATE; WATER; CAPRYLYL GLYCOL; SODIUM LAUROYL SARCOSINATE; COCAMIDOPROPYL HYDROXYSULTAINE; HECTORITE; SODIUM METHYL COCOYL TAURATE; GLUCONOLACTONE; SODIUM CHLORIDE; PEG-6 CAPRYLIC/CAPRIC GLYCERIDES; BENZOIC ACID; CERAMIDE NP; TETRASODIUM GLUTAMATE DIACETATE; CERAMIDE AP; PHYTOSPHINGOSINE; ETHYLHEXYLGLYCERIN

Target Up and Up Salicylic Acid Acne Wash

Active ingredient

Salicylic Acid 2.0%

Purpose

Acne Treatment

Uses

for the treatment of acne.

Warnings

For external use only

When using this product

• skin irritation and dryness is more likely to occur if you use another topical acne medication at the same time. If irritation occurs only use one topical acne medication at a time. • avoid contact with eyes. If contact occurs, flush thoroughly with water.

Keep out of reach of children.

If swallowed, get medical help or contact a Poison Control Center right away.

Directions

• cover the entire affected area with a thin layer and rinse thoroughly one to three times daily • if bothersome dryness or peeling occurs, reduce application to once a day or every other day • because excessive drying of the skin may occur, start with one application daily, then gradually increase to two or three times daily if needed or as directed by a doctor.

Other information

• may stain some fabric

Inactive ingredients

benzoic acid, caprylyl glycol, carbomer,
ceramide AP, ceramide EOP, ceramide NP, cholesterol, cocamidopropyl
hydroxysultaine, ethylhexylglycerin, gluconolactone, glycerin, hectorite,
hyaluronic acid, niacinamide, PEG-6 caprylic/capric glycerides, PEG-150
pentaerythrityl tetrastearate, phytosphingosine, sodium benzoate,
sodium chloride, sodium citrate, sodium hydroxide, sodium lauroyl
lactylate, sodium lauroyl sarcosinate, sodium methyl cocoyl taurate,
tetrasodium glutamate diacetate, water, xanthan gum.